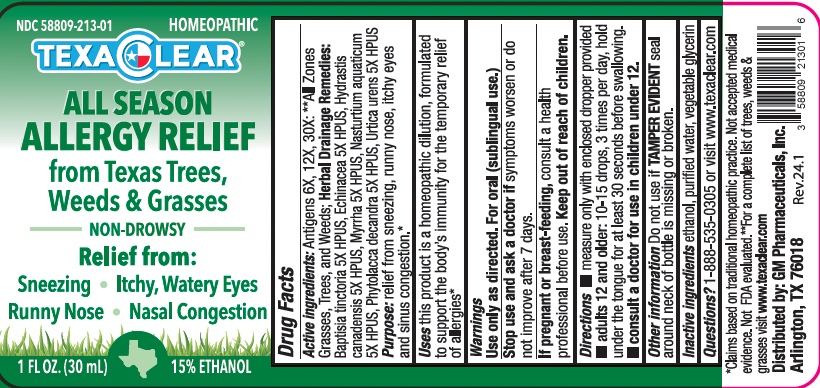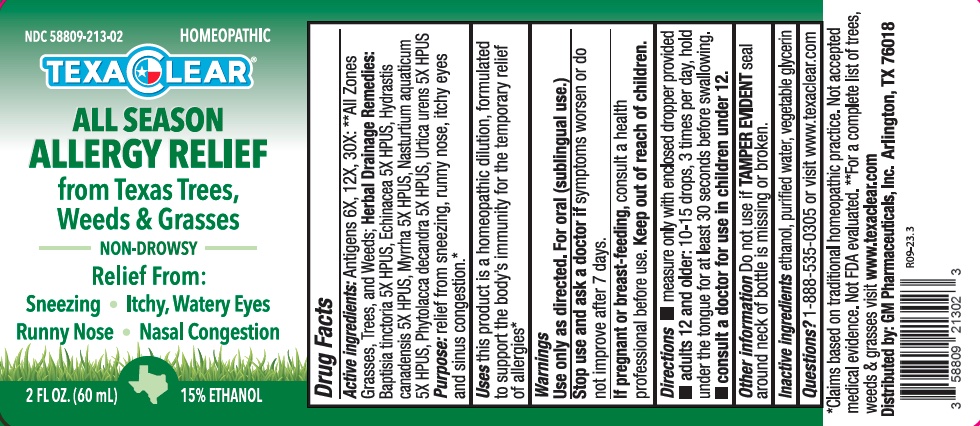 DRUG LABEL: TexaClear All Season Allergy Relief
NDC: 58809-213 | Form: SOLUTION/ DROPS
Manufacturer: GM Pharmaceuticals, INC
Category: homeopathic | Type: HUMAN OTC DRUG LABEL
Date: 20251209

ACTIVE INGREDIENTS: HOLCUS LANATUS POLLEN 6 [hp_X]/1 mL; MORUS RUBRA POLLEN 6 [hp_X]/1 mL; PINUS STROBUS POLLEN 6 [hp_X]/1 mL; NASTURTIUM OFFICINALE 5 [hp_X]/1 mL; AMARANTHUS SPINOSUS POLLEN 6 [hp_X]/1 mL; FRAXINUS AMERICANA POLLEN 6 [hp_X]/1 mL; JUGLANS NIGRA POLLEN 6 [hp_X]/1 mL; JUNIPERUS VIRGINIANA POLLEN 6 [hp_X]/1 mL; PLATANUS OCCIDENTALIS POLLEN 6 [hp_X]/1 mL; POPULUS DELTOIDES SUBSP. DELTOIDES POLLEN 6 [hp_X]/1 mL; POPULUS DELTOIDES SUBSP. MONILIFERA POLLEN 6 [hp_X]/1 mL; QUERCUS RUBRA POLLEN 6 [hp_X]/1 mL; SORGHUM HALEPENSE POLLEN 6 [hp_X]/1 mL; TRITICUM AESTIVUM POLLEN 6 [hp_X]/1 mL; URTICA DIOICA POLLEN 6 [hp_X]/1 mL; AMBROSIA PSILOSTACHYA POLLEN 6 [hp_X]/1 mL; RUMEX CRISPUS POLLEN 6 [hp_X]/1 mL; SECALE CEREALE POLLEN 6 [hp_X]/1 mL; TAXODIUM DISTICHUM POLLEN 6 [hp_X]/1 mL; XANTHIUM STRUMARIUM POLLEN 6 [hp_X]/1 mL; QUERCUS NIGRA POLLEN 6 [hp_X]/1 mL; QUERCUS STELLATA POLLEN 6 [hp_X]/1 mL; SOLIDAGO CANADENSIS POLLEN 6 [hp_X]/1 mL; AMARANTHUS RETROFLEXUS POLLEN 6 [hp_X]/1 mL; AMBROSIA CONFERTIFLORA POLLEN 6 [hp_X]/1 mL; EUCALYPTUS GLOBULUS POLLEN 6 [hp_X]/1 mL; MYRRH 5 [hp_X]/1 mL; SALSOLA KALI POLLEN 6 [hp_X]/1 mL; QUERCUS MACROCARPA POLLEN 6 [hp_X]/1 mL; SYAGRUS ROMANZOFFIANA POLLEN 6 [hp_X]/1 mL; ZEA MAYS POLLEN 6 [hp_X]/1 mL; CHENOPODIUM ALBUM POLLEN 6 [hp_X]/1 mL; ARTEMISIA TRIDENTATA POLLEN 6 [hp_X]/1 mL; GOLDENSEAL 5 [hp_X]/1 mL; FAGUS GRANDIFOLIA POLLEN 6 [hp_X]/1 mL; FRAXINUS VELUTINA POLLEN 6 [hp_X]/1 mL; BROUSSONETIA PAPYRIFERA POLLEN 6 [hp_X]/1 mL; PINUS ECHINATA POLLEN 6 [hp_X]/1 mL; URTICA URENS WHOLE 5 [hp_X]/1 mL; AMARANTHUS PALMERI POLLEN 6 [hp_X]/1 mL; AMARANTHUS TUBERCULATUS POLLEN 6 [hp_X]/1 mL; CARYA ILLINOINENSIS POLLEN 6 [hp_X]/1 mL; LIQUIDAMBAR STYRACIFLUA POLLEN 6 [hp_X]/1 mL; MELALEUCA QUINQUENERVIA POLLEN 6 [hp_X]/1 mL; MORUS ALBA POLLEN 6 [hp_X]/1 mL; HESPEROCYPARIS ARIZONICA POLLEN 6 [hp_X]/1 mL; JUNIPERUS OCCIDENTALIS POLLEN 6 [hp_X]/1 mL; OLEA EUROPAEA POLLEN 6 [hp_X]/1 mL; ECHINACEA ANGUSTIFOLIA ROOT 5 [hp_X]/1 mL; ACER SACCHARUM POLLEN 6 [hp_X]/1 mL; ANTHOXANTHUM ODORATUM POLLEN 6 [hp_X]/1 mL; AVENA SATIVA POLLEN 6 [hp_X]/1 mL; PHYTOLACCA AMERICANA ROOT 5 [hp_X]/1 mL; BAPTISIA TINCTORIA ROOT 5 [hp_X]/1 mL; ACER NEGUNDO POLLEN 6 [hp_X]/1 mL; AMBROSIA ACANTHICARPA POLLEN 6 [hp_X]/1 mL; AMBROSIA ARTEMISIIFOLIA POLLEN 6 [hp_X]/1 mL; AMBROSIA TRIFIDA POLLEN 6 [hp_X]/1 mL; ARTEMISIA VULGARIS POLLEN 6 [hp_X]/1 mL; CARYA OVATA POLLEN 6 [hp_X]/1 mL; CELTIS OCCIDENTALIS POLLEN 6 [hp_X]/1 mL; CYCLACHAENA XANTHIFOLIA POLLEN 6 [hp_X]/1 mL; JUNIPERUS ASHEI POLLEN 6 [hp_X]/1 mL; LIGUSTRUM VULGARE POLLEN 6 [hp_X]/1 mL; MYRICA CERIFERA POLLEN 6 [hp_X]/1 mL; POA PRATENSIS POLLEN 6 [hp_X]/1 mL; POPULUS ALBA POLLEN 6 [hp_X]/1 mL; RUMEX ACETOSELLA POLLEN 6 [hp_X]/1 mL; SALIX NIGRA POLLEN 6 [hp_X]/1 mL; SCHINUS MOLLE POLLEN 6 [hp_X]/1 mL; ACACIA DEALBATA POLLEN 6 [hp_X]/1 mL; ATRIPLEX WRIGHTII POLLEN 6 [hp_X]/1 mL; PASPALUM NOTATUM POLLEN 6 [hp_X]/1 mL; POPULUS NIGRA POLLEN 6 [hp_X]/1 mL; QUERCUS ALBA POLLEN 6 [hp_X]/1 mL; QUERCUS GAMBELII POLLEN 6 [hp_X]/1 mL; PLANTAGO LANCEOLATA POLLEN 6 [hp_X]/1 mL; PROSOPIS JULIFLORA POLLEN 6 [hp_X]/1 mL; QUERCUS VIRGINIANA POLLEN 6 [hp_X]/1 mL; ULMUS AMERICANA POLLEN 6 [hp_X]/1 mL; AMBROSIA BIDENTATA POLLEN 6 [hp_X]/1 mL; BASSIA SCOPARIA POLLEN 6 [hp_X]/1 mL; BETULA NIGRA POLLEN 6 [hp_X]/1 mL; DISTICHLIS SPICATA POLLEN 6 [hp_X]/1 mL; EUPATORIUM CAPILLIFOLIUM POLLEN 6 [hp_X]/1 mL
INACTIVE INGREDIENTS: ALCOHOL; GLYCERIN; WATER

TexaClear All Season Allergy Relief (Homeopathic)

Active ingredients

Antigens 6X, 12X, 30X: **All Zones Grasses, Trees, and Weeds; Herbal Drainage Remedies: Baptisia tinctoria 5X HPUS, Echinacea 5X HPUS, Hydrastis canadensis 5X HPUS, Myrrha 5X HPUS, Nasturtium aquaticum 5X HPUS, Phytolacca decandra 5X HPUS, Urtica urens 5X HPUS

Purpose

Relief from sneezing, runny nose, itchy eyes and sinus congestion.*

Uses

This product is a homeopathic dilution, formulated to support the body's immunity for the temporary relief of allergies.*

Warnings

Use only as directed.

For oral (sublingual use).

Stop use and ask a doctor if

symptoms worsen or do not improve after 7 days.

If pregnant or breast-feeding,

consult a health professional before use.

Directions

- Measure only with enclosed dropper provided.
- Adults 12 years and older: 10-15 drops, 3 times per day, hold under the tongue for at least 30 seconds before swallowing.
- Consult a doctor for use in children under 12

Other information

Do not use if TAMPER EVIDENT seal around neck of bottle is missing or broken.

Inactive ingredients

ethanol, purified water, vegetable glycerin

Questions?

1-888-535-0305 or visit www.texaclear.com

HEALTH CLAIM

* Claims based on traditional homeopathic practice. Not accepted medical evidence. Not FDA evaluated.

** For a complete list of trees, weeds & grasses visit www.texaclear.com

Distributed by: GM Pharmaceuticals, Inc. Arlington, TX 76018

NDC 58809-213-02

HOMEOPATHIC

TEXACLEAR

ALL SEASON

ALLERGY RELIEF

from Texas Trees,

Weeds & Grasses

Non-Drowsy

Relief from:

Sneezing • Itchy, Watery Eyes

Runny Nose • Nasal Congestion

2 fl oz. (60 mL) 15% ETHANOL

NDC 58809-213-01

HOMEOPATHIC

TEXACLEAR

ALL SEASON

ALLERGY RELIEF

from Texas Trees,

Weeds & Grasses

Non-Drowsy

Relief from:

Sneezing • Itchy, Watery Eyes

Runny Nose • Nasal Congestion

1 fl oz. (30 mL) 15% ETHANOL